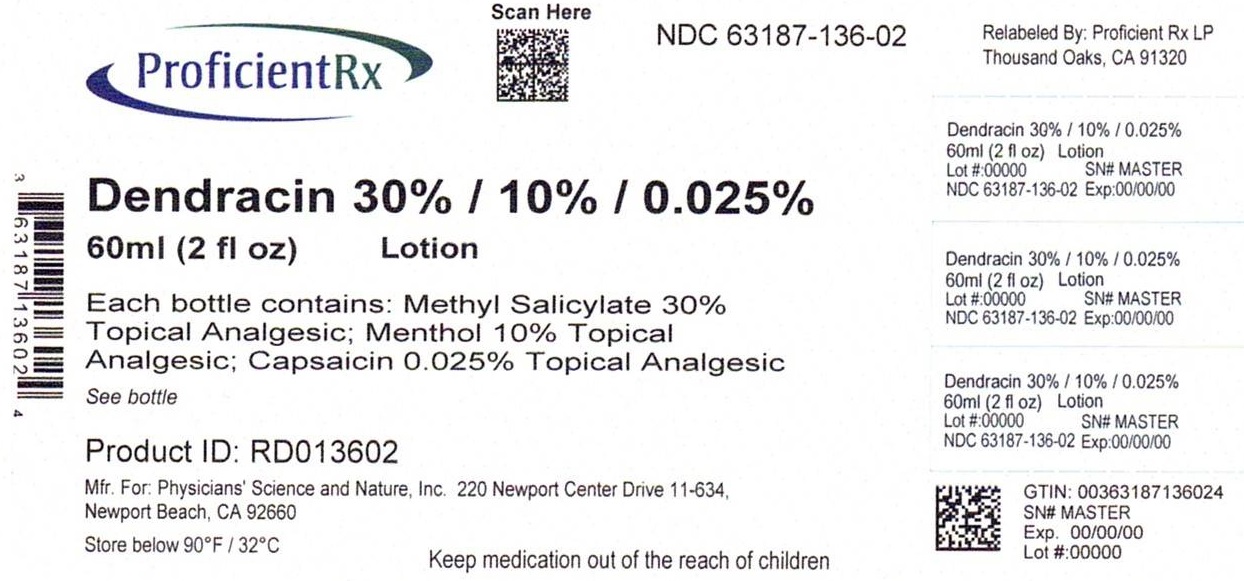 DRUG LABEL: Dendracin Neurodendraxcin
NDC: 63187-136 | Form: LOTION
Manufacturer: Proficient Rx LP
Category: otc | Type: HUMAN OTC DRUG LABEL
Date: 20240101

ACTIVE INGREDIENTS: METHYL SALICYLATE 18 g/60 mL; MENTHOL, UNSPECIFIED FORM 6 g/60 mL; CAPSAICIN 0.015 g/60 mL
INACTIVE INGREDIENTS: WATER; BENZOCAINE; GLYCERYL MONOSTEARATE; PEG-100 STEARATE; STEARIC ACID; PROPYLENE GLYCOL; CETYL ALCOHOL; DIMETHYL SULFOXIDE; POLOXAMER 407; ALOE VERA LEAF; BORAGE SEED OIL; AMMONIO METHACRYLATE COPOLYMER TYPE A; GINGER; LECITHIN, SOYBEAN; METHYLPARABEN; PROPYLPARABEN; DMDM HYDANTOIN; SODIUM STEAROYL GLUTAMATE; TROLAMINE

Dendracin Neurodendraxcin®, Topical Pain Relief Lotion

Active ingredients

Methyl Salicylate 30%

Menthol 10%

Capsaicin 0.025%

Purpose

Topical Analgesic

Uses:

For temporary relief of mild pain due to muscular strain, arthritis, and simple back pain. Does not cure any disease.

Warnings:

For external use only. Do not use in eyes, mouth, on mucous membranes, or genitals. Do not tightly bandage. Do not use with heating pad. Do not use with other topical pain products.

Directions:

Use only as directed. Shake before each use. Prior to first use, rub small amount to check for sensitivity. Gently rub over painful areas. Dry before contact with clothes or bedding to avoid staining. Wash hands after use. Do not use more than 4 times daily or if pregnant or nursing. If swallowed, call poison control. If placed into eyes, rinse with cold water and call a doctor.

Do Not Use:

On cuts or infected skin, on children less than 12 years old, in large amounts, especially over raw or blistered skin, if allergic to any ingredients, PABA, aspirin products, or sulfa.

Store below 90°F/32°C.

Stop Use and Ask a Physician:

For severe undiagnosed pain. If pain worsens or persist for more than 7 days. If pain clears up and then recurs in a few days. If itching or rash occurs.

Inactive ingredients:

Water, benzocaine, glyceryl stearate, PEG 100 stearate, stearic acid, cetyl alcohol, propylene glycol, dimethyl sulfoxide, triethanolamine, poloxamer 407, aloe barbadensis gel, borage oil, ammonium acryloyldimethyltaurate, zingiber officinale root extract, methylparaben, propylparaben, soya lecithin, DMDM hydantoin, sodium stearoyl glutamate.

Manufactured for Physicians' Science and Nature, Inc.

220 Newport Center Drive 11-634, Newport Beach, CA 92660

Made in the USA

Patent Pending

Relabeled by:

Proficient Rx LP

Thousand Oaks, CA 91320